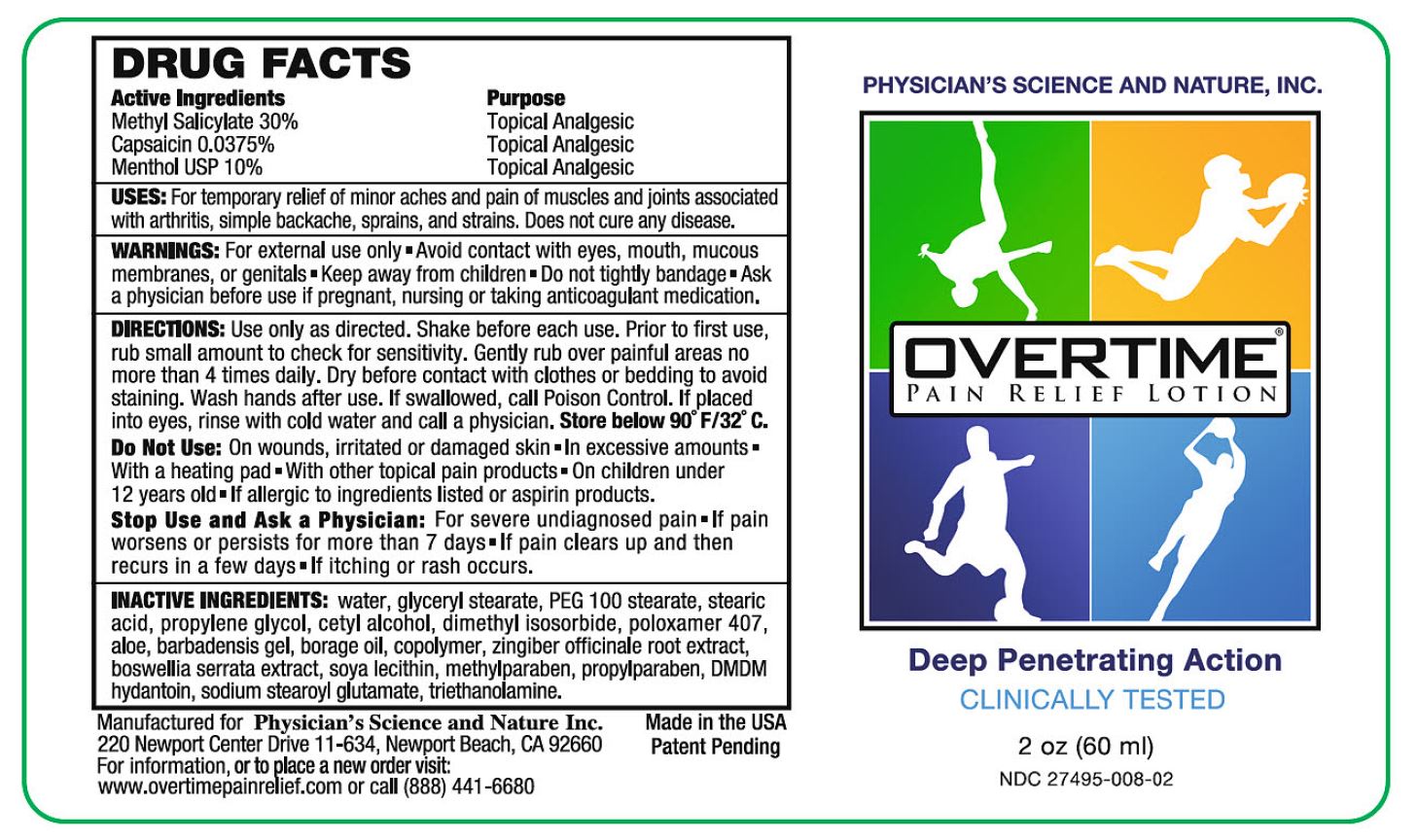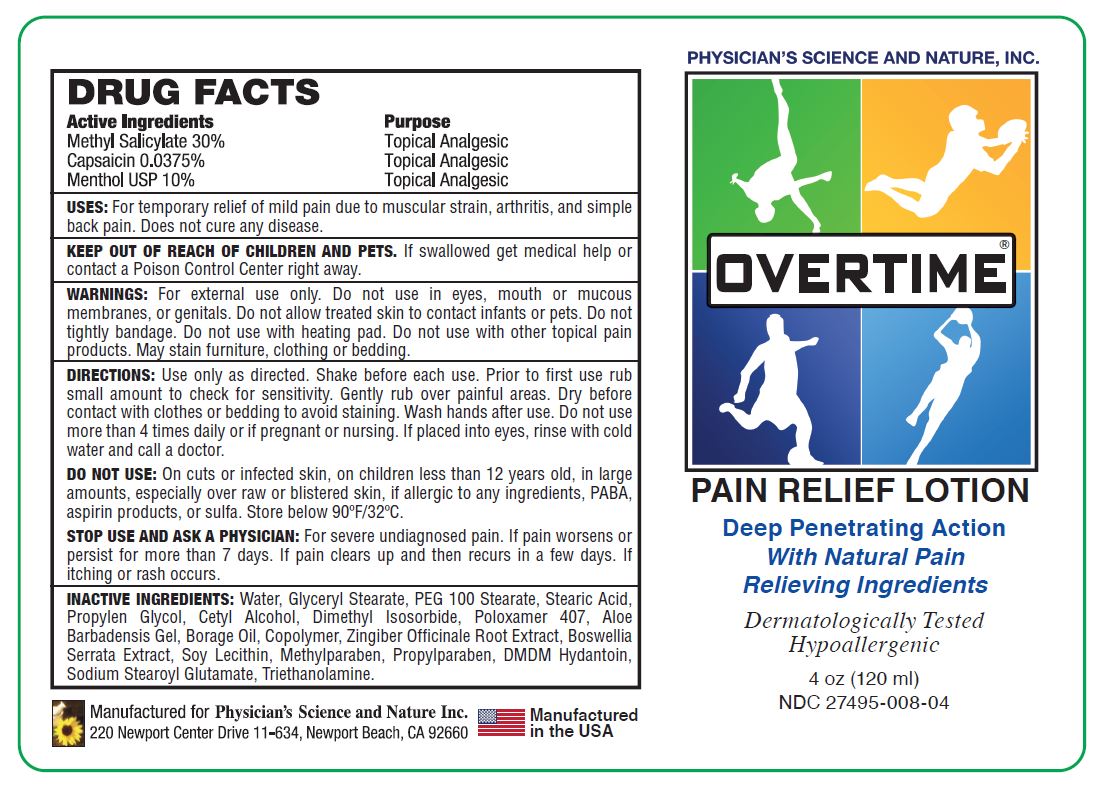 DRUG LABEL: Overtime
NDC: 27495-008 | Form: LOTION
Manufacturer: Physicians Science & Nature Inc.
Category: otc | Type: HUMAN OTC DRUG LABEL
Date: 20251110

ACTIVE INGREDIENTS: METHYL SALICYLATE 18 g/60 mL; MENTHOL 6 g/60 mL; CAPSAICIN 0.0225 g/60 mL
INACTIVE INGREDIENTS: WATER; GLYCERYL MONOSTEARATE; PEG-100 STEARATE; STEARIC ACID; PROPYLENE GLYCOL; CETYL ALCOHOL; DIMETHYL ISOSORBIDE; POLOXAMER 407; ALOE VERA LEAF; BORAGE SEED OIL; GINGER; INDIAN FRANKINCENSE; LECITHIN, SOYBEAN; METHYLPARABEN; PROPYLPARABEN; DMDM HYDANTOIN; TROLAMINE; SODIUM STEAROYL GLUTAMATE

Overtime®Pain Relief Lotion

Active Ingredients

Methyl Salicylate 30%

Capsaicin 0.0375%

Menthol USP 10%

Purpose

Topical Analgesic

USES:

For temporary relief of mild pain due to muscular strain, arthritis, and simple back pain. Does not cure any disease.

KEEP OUT OF REACH OF CHILDREN AND PETS.

If swallowed get medical help or contact a Poison Control Center right away.

WARNINGS:

For external use only. Do not use in eyes, mouth or mucous membranes, or genitals. Do not allow treated skin to contact infants or pets. Do not tightly bandage. Do not use with heating pad. Do not use with other topical pain products. May stain furniture, clothing or bedding.

DIRECTIONS:

Use only as directed. Shake before each use. Prior to first use, rub small amount to check for sensitivity. Gently rub over painful areas. Dry before contact with clothes or bedding to avoid staining. Wash hands after use. Do not use more than 4 times daily or if pregnant or nursing. If placed into eyes, rinse with cold water and call a doctor.

DO NOT USE:

On cuts or infected skin, on children less than 12 years old, in large amounts, especially over raw or blistered skin, if allergic to any ingredients, PABA, aspirin products, or sulfa. Store below 90°F/32°C.

STOP USE AND ASK A PHYSICIAN:

For severe undiagnosed pain. If pain worsens or persist for more than 7 days. If pain clears up and then recurs in a few days. If itching or rash occurs.

INACTIVE INGREDIENTS:

water, glyceryl Stearate, PEG 100 Stearate, Stearic Acid, Propylene Glycol, Cetyl Alcohol, Dimethyl Isosorbide, Poloxamer 407, Aloe Barbadensis Gel, Borage Oil, Copolymer, Zingiber Officinale Root Extract, Boswellia Serrata Extract, Soy Lecithin, Methylparaben, Propylparaben, DMDM Hydantoin, Sodium Stearoyl Glutamate, Triethanolamine.

Manufactured for Physician's Science and Nature Inc.
220 Newport Center Drive 11-634, Newport Beach, CA 92660
Manufactured in the USA

PHYSICIAN'S SCIENCE AND NATURE, INC.

OVERTIME®

PAIN RELIEF LOTION

Deep Penetrating Action

With Natural Pain Relieving Ingredients

Dermatologically Tested

Hypoallergenic

NDC 27495-008-02

2 Oz. Label

NDC 27495-008-04

4 Oz. Label